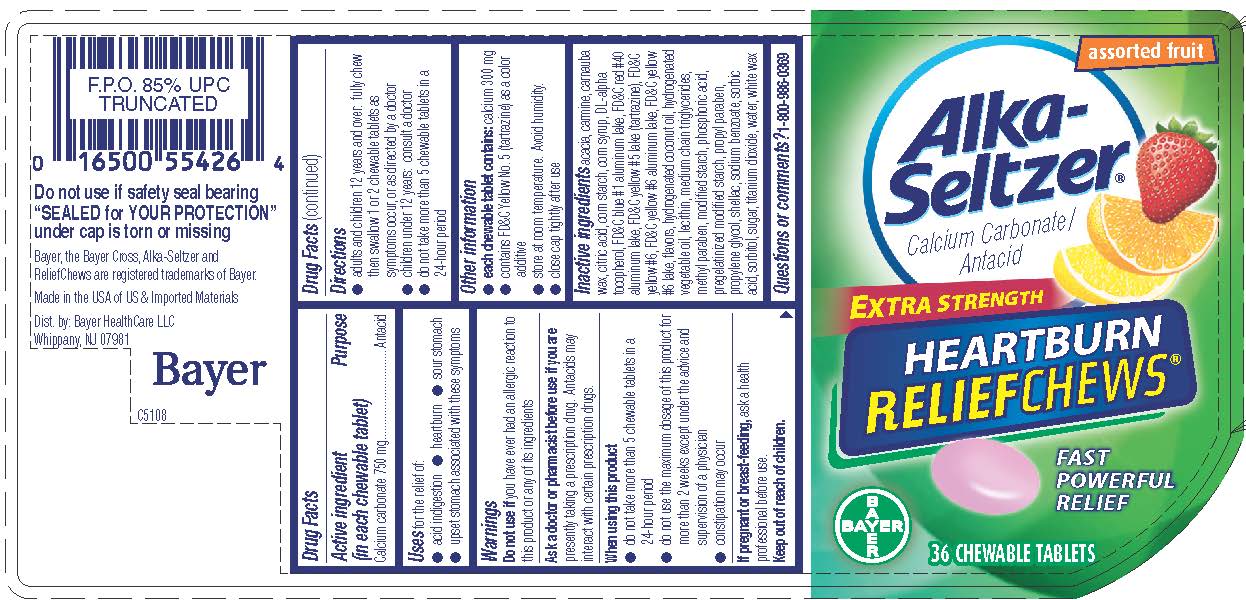 DRUG LABEL: Alka-Seltzer Heartburn ReliefChews
NDC: 0280-0221 | Form: TABLET, CHEWABLE
Manufacturer: Bayer HealthCare LLC.
Category: otc | Type: HUMAN OTC DRUG LABEL
Date: 20251204

ACTIVE INGREDIENTS: CALCIUM CARBONATE 750 mg/1 1
INACTIVE INGREDIENTS: YELLOW WAX; ACACIA; CARNAUBA WAX; CITRIC ACID MONOHYDRATE; STARCH, CORN; CORN SYRUP; .ALPHA.-TOCOPHEROL, DL-; FD&C BLUE NO. 1; ALUMINUM OXIDE; FD&C RED NO. 40; FD&C YELLOW NO. 5; FD&C YELLOW NO. 6; HYDROGENATED COCONUT OIL; MEDIUM-CHAIN TRIGLYCERIDES; METHYLPARABEN; PHOSPHORIC ACID; PROPYLPARABEN; PROPYLENE GLYCOL; WATER; SHELLAC; SODIUM BENZOATE; SORBIC ACID; SORBITOL; LECITHIN, SOYBEAN; SUCROSE; TITANIUM DIOXIDE

Alka-Seltzer® Heartburn ReliefChews™

Drug Facts

Active ingredient (in each chewable tablet)

Calcium carbonate 750 mg

Purpose

Antacid

Uses

for the relief of:

- acid indigestion
- heartburn
- sour stomach
- upset stomach associated with these symptoms

Warnings

Do not use if you have ever had an allergic reaction to this product or any of its ingredients

Ask a doctor or pharmacist before use if you are presently taking a prescription drug. Antacids may interact with certain prescription drugs.

When using this product

- do not take more than 10 chewable tablets in a 24-hour period
- do not use the maximum dosage of this product for more than 2 weeks except under the advice and supervision of a physician
- constipation may occur

PREGNANCY OR BREAST FEEDING

If pregnant or breast-feeding, ask a health professional before use.

Keep out of reach of children.

Directions

- adults and children 12 years and over: chew and swallow 1-2 chewable tablets every 2 to 4 hours as symptoms occur, or as directed by a doctor
- children under 12 years: consult a doctor
- do not take more than 10 chewable tablets in a 24-hour period

Other information

- each chewable tablet contains: calcium 300 mg
- contains FD&C Yellow No. 5 (tartrazine) as a color additive
- store at room temperature. Avoid humidity. Close cap tightly after use.

Inactive ingredients

acacia, beeswax, carmine, carnauba wax, citric acid, corn starch, corn syrup, DL-alpha tocopherol, FD&C blue #1 aluminum lake, FD&C red #40 aluminum lake, FD&C yellow #5 lake (tartrazine), FD&C yellow #6, FD&C yellow #6 aluminum lake, FD&C yellow #6 lake, flavors, hydrogenated coconut oil, medium chain triglycerides, methyl paraben, modified starch, phosphoric acid, pregelatinized modified starch, propyl paraben, propylene glycol, purified water, shellac, sodium benzoate, sorbic acid, sorbitol, soy lecithin, sucrose, titanium dioxide

Questions?

1-800-986-0369 (Mon – Fri 9AM – 5PM EST) or www.alkaseltzer.com

Dist. by:
Bayer HealthCare LLC
Whippany, NJ 07981

PRINCIPAL DISPLAY PANEL - 36 Tablet Bottle Label

assorted fruit

Alka-
Seltzer ®
Calcium Carbonate /
Antacid

EXTRA STRENGTH

HEARTBURN
RELIEFCHEWS™

Fast Powerful Relief

36 CHEWABLE TABLETS